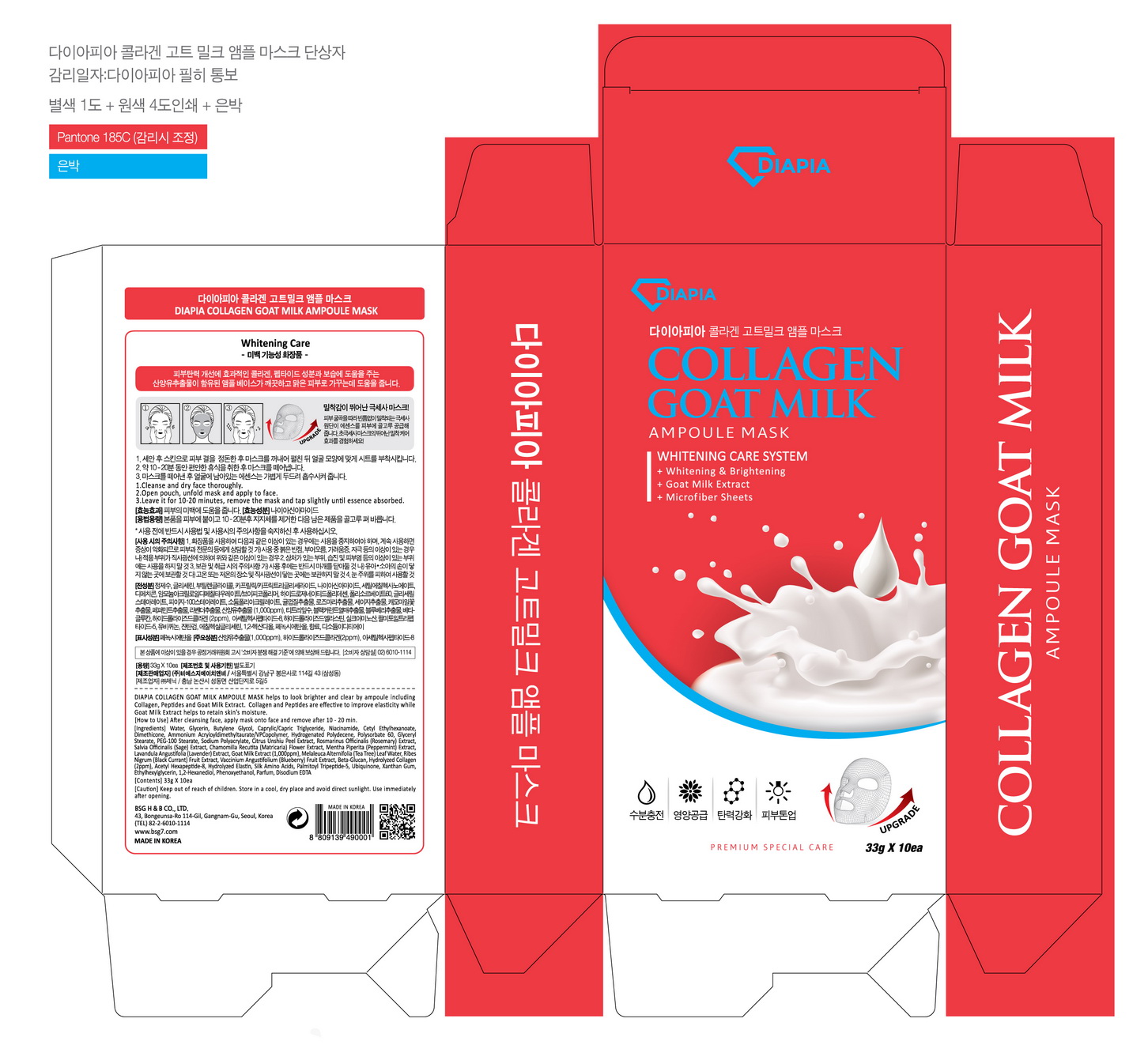 DRUG LABEL: DIAPIA Collagen Goat Milk Ampoule Mask
NDC: 71857-0003 | Form: LIQUID
Manufacturer: BSG H & B Co., Ltd.
Category: otc | Type: HUMAN OTC DRUG LABEL
Date: 20171114

ACTIVE INGREDIENTS: GLYCERIN 6 g/100 g
INACTIVE INGREDIENTS: BUTYLENE GLYCOL; NIACINAMIDE; WATER

ACTIVE INGREDIENT

glycerin

PURPOSE

whitening care

Keep out of reach of children

INDICATIONS AND USAGE

After cleansing face, apply mask onto face and remove after 20~40min

Keep out of reach of children.
Store in a cool, dry place and avoid direct sunlight.
Use immediately after opening

INACTIVE INGREDIENT

water, butylene glycol, niacinamide, etc

DOSAGE AND ADMINISTRATION

for external use only